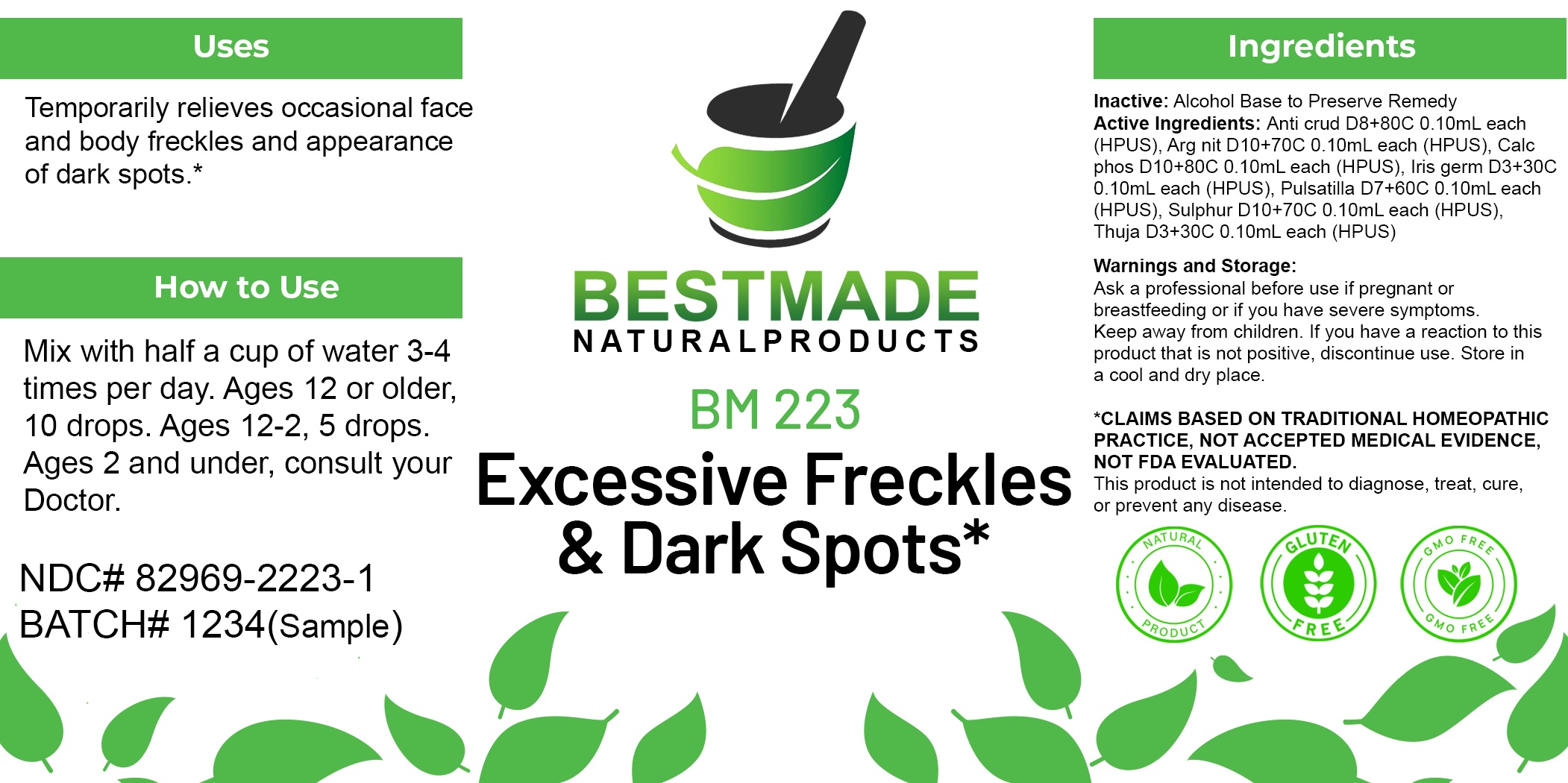 DRUG LABEL: Bestmade Natural Products BM223
NDC: 82969-2223 | Form: LIQUID
Manufacturer: Bestmade Natural Products
Category: homeopathic | Type: HUMAN OTC DRUG LABEL
Date: 20250303

ACTIVE INGREDIENTS: PULSATILLA VULGARIS 30 [hp_C]/30 [hp_C]; THUJA OCCIDENTALIS LEAFY TWIG 30 [hp_C]/30 [hp_C]; SILVER NITRATE 30 [hp_C]/30 [hp_C]; SULFUR 30 [hp_C]/30 [hp_C]; ANTIMONY TRISULFIDE 30 [hp_C]/30 [hp_C]; TRIBASIC CALCIUM PHOSPHATE 30 [hp_C]/30 [hp_C]; IRIS GERMANICA ROOT 30 [hp_C]/30 [hp_C]
INACTIVE INGREDIENTS: ALCOHOL 30 [hp_C]/30 [hp_C]

BM223

DOSAGE AND ADMINISTRATION

How to Use

Mix with half a cup of water 3-4 times per day. Ages 12 or older, 10 drops. Ages 12-2, 5 drops. Ages 2 and under, consult your Doctor.

Inactive:

Alcohol Base to Preserve Product

ACTIVE INGREDIENT

Active Ingredients: Anti crud D8+80C 0.10mL each (HPUS), Arg nit D10+70C 0.10mL each (HPUS), Calc phos D10+80C 0.10mL each (HPUS), Iris germ D3+30C 0.10mL each (HPUS), Pulsatilla D7+60C 0.10mL each (HPUS), Sulphur D10+70C 0.10mL each (HPUS), Thuja D3+30C 0.10mL each (HPUS)

KEEP OUT OF REACH OF CHILDREN

Warnings and Storage:

Ask a professional before use if pregnant or breastfeeding or if you have severe symptoms.

Keep away from children. If you have a reaction to this product that is not positive, discontinue use. Store in a cool and dry place

*CLAIMS BASED ON TRADITIONAL HOMEOPATHIC PRACTICE, NOT ACCEPTED MEDICAL EVIDENCE NOT FDA EVALUATED.
This product is not intended to diagnose, treat, cure, or prevent any disease.

Warnings and Storage:

Ask a professional before use if pregnant or breastfeeding or if you have severe symptoms.

Keep away from children. If you have a reaction to this product that is not positive, discontinue use. Store in a cool and dry place

*CLAIMS BASED ON TRADITIONAL HOMEOPATHIC PRACTICE, NOT ACCEPTED MEDICAL EVIDENCE NOT FDA EVALUATED.
This product is not intended to diagnose, treat, cure, or prevent any disease.

Uses
Temporarily relieves occasional face and body freckles and appearance of dark spots.*

Uses
Temporarily relieves occasional face and body freckles and appearance of dark spots.*

Entire package label.